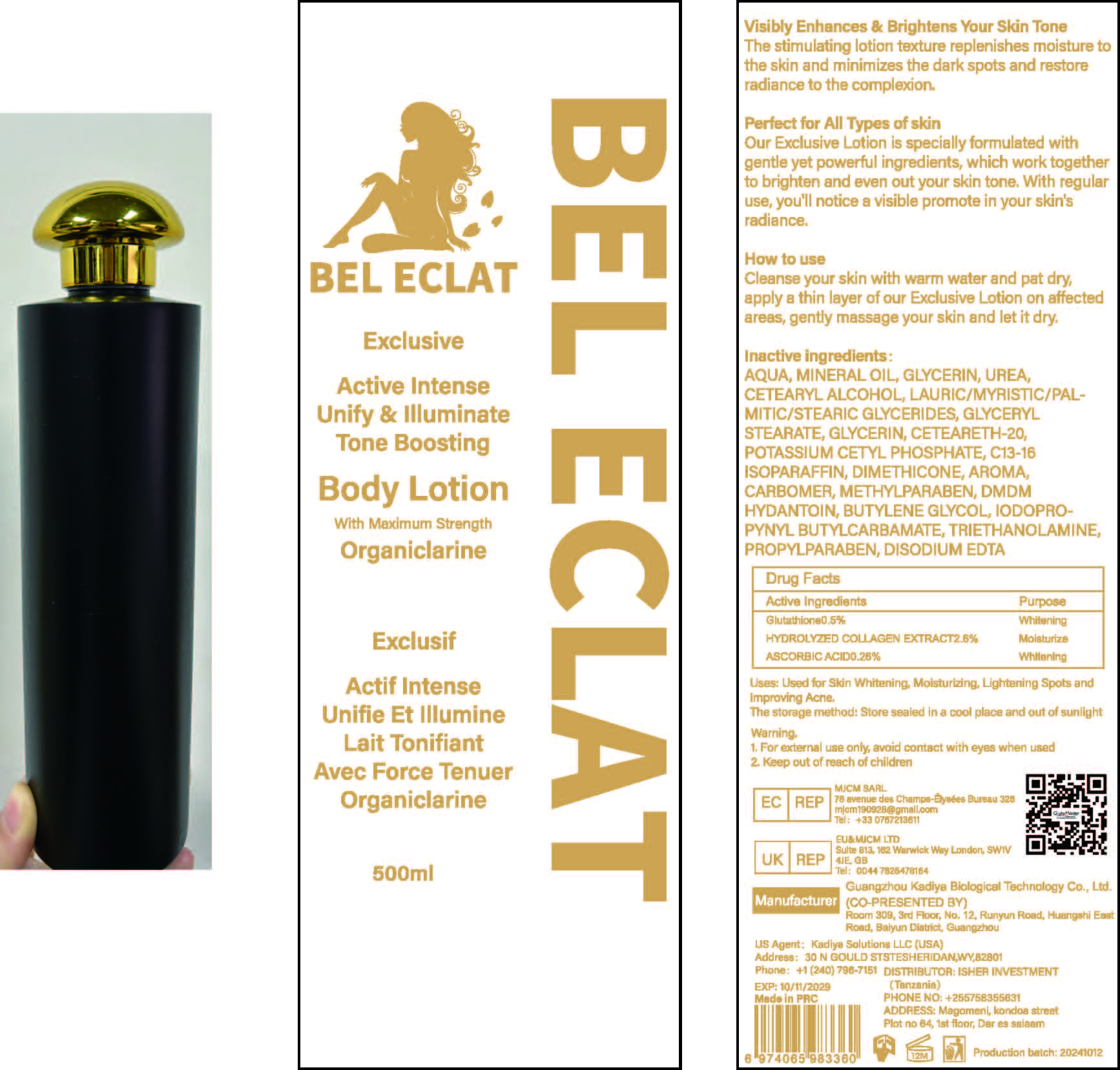 DRUG LABEL: IlluminateToneBoostingBodyLotion
NDC: 84423-060 | Form: EMULSION
Manufacturer: Guangzhou Kadiya Biotechnology Co., Ltd.
Category: otc | Type: HUMAN OTC DRUG LABEL
Date: 20241217

ACTIVE INGREDIENTS: ASCORBIC ACID 1.3 g/500 mL; GLUTATHIONE 2.5 g/500 mL
INACTIVE INGREDIENTS: UREA; POTASSIUM CETYL PHOSPHATE; EDETATE DISODIUM; MINERAL OIL; GLYCERYL STEARATE; CETEARETH-20; C13-16 ISOPARAFFIN; DIMETHICONE 1000; CARBOMER; METHYLPARABEN; GLYCERIN; CETEARYL ALCOHOL; BUTYLENE GLYCOL; TRIETHANOLAMINE; AQUA; DMDM HYDANTOIN; IODOPROPYNYL BUTYLCARBAMATE; PROPYLPARABEN

PURPOSE

Used for Skin Whitening, Moisturizing, Lightening Spots and Improving Acne.

INACTIVE INGREDIENT

AQUA，MINERAL OIL，GLYCERIN，UREA，CETEARYL ALCOHOL，LAURIC/MYRISTIC/PALMITIC/STEARIC GLYCERIDES，GLYCERYL STEARATE，GLYCERIN，CETEARETH-20，POTASSIUM CETYL PHOSPHATE，C13-16 ISOPARAFFIN，DIMETHICONE，AROMA，CARBOMER，METHYLPARABEN，DMDM HYDANTOIN，BUTYLENE GLYCOL，IODOPROPYNYL BUTYLCARBAMATE，TRIETHANOLAMINE，PROPYLPARABEN，DISODIUM EDTA

WARNINGS

1、For external use only, avoid contact with eyes when used
2、Keep out of reach of children

INDICATIONS AND USAGE

Visibly Enhances & Brightens Your Skin ToneThe stimulating lotion texture replenishes moisture to the skin and minimizes the dark spots and restore radiance to the complexion.

DOSAGE AND ADMINISTRATION

Cleanse your skin with warm water and pat dry. apply a thin layer of our Exclusive Lotion on affected areas, gently massage your skin and let it dry.

KEEP OUT OF REACH OF CHILDREN SECTION

ACTIVE INGREDIENT

AQUA，MINERAL OIL，GLYCERIN，UREA，CETEARYL ALCOHOL，LAURIC/MYRISTIC/PALMITIC/STEARIC GLYCERIDES，GLYCERYL STEARATE，GLYCERIN，CETEARETH-20，POTASSIUM CETYL PHOSPHATE，C13-16 ISOPARAFFIN，DIMETHICONE，AROMA，CARBOMER，METHYLPARABEN，DMDM HYDANTOIN，BUTYLENE GLYCOL，IODOPROPYNYL BUTYLCARBAMATE，TRIETHANOLAMINE，PROPYLPARABEN，DISODIUM EDTA

PACKAGE LABEL

Active Ingredients Purpose
Glutathione0.5% Whitening
HYDROLYZED COLLAGEN EXTRACT2.6% Moisturize
ASCORBIC ACID0.26% Whitening

Uses：
Used for Skin Whitening, Moisturizing, Lightening Spots and Improving Acne.
The storage method：
Store sealed in a cool place and out of sunlight

Warning.
1、For external use only, avoid contact with eyes when used
2、Keep out of reach of children

Inactive ingredients：
AQUA，MINERAL OIL，GLYCERIN，UREA，CETEARYL ALCOHOL，LAURIC/MYRISTIC/PALMITIC/STEARIC GLYCERIDES，GLYCERYL STEARATE，GLYCERIN，CETEARETH-20，POTASSIUM CETYL PHOSPHATE，C13-16 ISOPARAFFIN，DIMETHICONE，AROMA，CARBOMER，METHYLPARABEN，DMDM HYDANTOIN，BUTYLENE GLYCOL，IODOPROPYNYL BUTYLCARBAMATE，TRIETHANOLAMINE，PROPYLPARABEN，DISODIUM EDTA